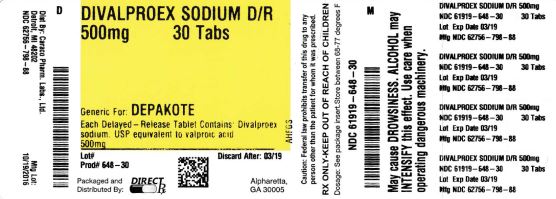 DRUG LABEL: DIVALPROEX SODIUM
NDC: 61919-648 | Form: TABLET, DELAYED RELEASE
Manufacturer: DIRECT RX
Category: prescription | Type: HUMAN PRESCRIPTION DRUG LABEL
Date: 20200120

ACTIVE INGREDIENTS: DIVALPROEX SODIUM 500 mg/1 1
INACTIVE INGREDIENTS: SILICON DIOXIDE; STARCH, CORN; POVIDONE K30; HYPROMELLOSES; TITANIUM DIOXIDE; TRIACETIN; METHACRYLIC ACID - ETHYL ACRYLATE COPOLYMER (1:1) TYPE A; TALC; TRIETHYL CITRATE; SODIUM BICARBONATE; SODIUM LAURYL SULFATE; D&C RED NO. 30; FD&C BLUE NO. 2; FERRIC OXIDE RED

DIVALPROEX SODIUM

BOXED WARNING SECTION

HEPATIC FAILURE RESULTING IN FATALITIES HAS OCCURRED IN PATIENTS RECEIVING VALPROIC ACID AND ITS DERIVATIVES. EXPERIENCE HAS INDICATED THAT CHILDREN UNDER THE AGE OF TWO YEARS ARE AT A CONSIDERABLY INCREASED RISK OF DEVELOPING FATAL HEPATOTOXICITY, ESPECIALLY THOSE ON MULTIPLE ANTICONVULSANTS, THOSE WITH CONGENITAL METABOLIC DISORDERS, THOSE WITH SEVERE SEIZURE DISORDERS ACCOMPANIED BY MENTAL RETARDATION, AND THOSE WITH ORGANIC BRAIN DISEASE. WHEN DIVALPROEX SODIUM DELAYED-RELEASE TABLETS ARE USED IN THIS PATIENT GROUP, IT SHOULD BE USED WITH EXTREME CAUTION AND AS A SOLE AGENT. THE BENEFITS OF THERAPY SHOULD BE WEIGHED AGAINST THE RISKS. ABOVE THIS AGE GROUP, EXPERIENCE IN EPILEPSY HAS INDICATED THAT THE INCIDENCE OF FATAL HEPATOTOXICITY DECREASES CONSIDERABLY IN PROGRESSIVELY OLDER PATIENT GROUPS.

THESE INCIDENTS USUALLY HAVE OCCURRED DURING THE FIRST SIX MONTHS OF TREATMENT, SERIOUS OR FATAL HEPATOTOXICITY MAY BE PRECEDED BY NON-SPECIFIC SYMPTOMS SUCH AS MALAISE, WEAKNESS, LETHARGY, FACIAL EDEMA, ANOREXIA, AND VOMITING. IN PATIENTS WITH EPILEPSY, A LOSS OF SEIZURE CONTROL MAY ALSO OCCUR. PATIENTS SHOULD BE MONITORED CLOSELY FOR APPEARANCE OF THESE SYMPTOMS. LIVER FUNCTION TESTS SHOULD BE PERFORMED PRIOR TO THERAPY AND AT FREQUENT INTERVALS THEREAFTER, ESPECIALLY DURING THE FIRST SIX MONTHS.

TERATOGENICITY

VALPROATE CAN PRODUCE TERATOGENIC EFFECTS SUCH AS NEURAL TUBE DEFECTS (E.G., SPINA BIFIDA). ACCORDINGLY, THE USE OF DIVALPROEX SODIUM DELAYED-RELEASE TABLETS IN WOMEN OF CHILDBEARING POTENTIAL REQUIRES THAT THE BENEFITS OF ITS USE BE WEIGHED AGAINST THE RISK OF INJURY TO THE FETUS. THIS IS ESPECIALLY IMPORTANT WHEN THE TREATMENT OF A SPONTANEOUSLY REVERSIBLE CONDITION NOT ORDINARILY ASSOCIATED WITH PERMANENT INJURY OR RISK OF DEATH (E.G., MIGRAINE) IS CONTEMPLATED. SEE WARNINGS, INFORMATION FOR PATIENTS.

A PATIENT INFORMATION LEAFLET DESCRIBING THE TERATOGENIC POTENTIAL OF VALPROATE IS AVAILABLE FOR PATIENTS.

PANCREATITIS

CASES OF LIFE-THREATENING PANCREATITIS HAVE BEEN REPORTED IN BOTH CHILDREN AND ADULTS RECEIVING VALPROATE. SOME OF THE CASES HAVE BEEN DESCRIBED AS HEMORRHAGIC WITH A RAPID PROGRESSION FROM INITIAL SYMPTOMS TO DEATH. CASES HAVE BEEN REPORTED SHORTLY AFTER INITIAL USE AS WELL AS AFTER SEVERAL YEARS OF USE. PATIENTS AND GUARDIANS SHOULD BE WARNED THAT ABDOMINAL PAIN, NAUSEA, VOMITING, AND/OR ANOREXIA CAN BE SYMPTOMS OF PANCREATITIS THAT REQUIRE PROMPT MEDICAL EVALUATION. IF PANCREATITIS IS DIAGNOSED, VALPROATE SHOULD ORDINARILY BE DISCONTINUED. ALTERNATIVE TREATMENT FOR THE UNDERLYING MEDICAL CONDITION SHOULD BE INITIATED AS CLINICALLY INDICATED. (See WARNINGS and PRECAUTIONS.)

DESCRIPTION SECTION

Divalproex sodium is a stable coordination compound comprised of sodium valproate and valproic acid in a 1:1 molar relationship. Chemically it is designated as sodium hydrogen bis(2-propylpentanoate).
Divalproex sodium occurs as a white powder with a characteristic odor. Divalproex sodium delayed-release tablets are for oral administration. Divalproex sodium delayed-release tablets, USP are supplied in three dosage strengths containing divalproex sodium USP equivalent to 125 mg, 250 mg, or 500 mg of valproic acid.

Inactive Ingredients

Divalproex sodium delayed-release tablets: colloidal silicon dioxide, corn starch, povidone, pregelatinized maize starch, hypromellose, titanium dioxide, triacetin, methacrylic acid copolymer type C, talc, triethyl citrate, colloidal anhydrous silica, sodium bicarbonate, and sodium lauryl sulfate.

Imprinting ink contains shellac glaze, iron oxide black, N-butyl alcohol, propylene glycol, and ammonium hydroxide.

In addition, individual tablets contain:

125 mg tablets: FD&C Red #40, and FD&C Blue #2

250 mg tablets: FD&C Yellow #6, and iron oxide yellow

500 mg tablets: D&C Red #30, FD&C Blue #2, and iron oxide red

CLINICAL PHARMACOLOGY SECTION

Pharmacodynamics

Divalproex sodium dissociates to the valproate ion in the gastrointestinal tract. The mechanisms by which valproate exerts its therapeutic effects have not been established. It has been suggested that its activity in epilepsy is related to increased brain concentrations of gamma-aminobutyric acid (GABA).

PharmacokineticsAbsorption/Bioavailability

Equivalent oral doses of divalproex sodium delayed-release tablets (divalproex sodium) products and valproic acid capsules deliver equivalent quantities of valproate ion systemically. Although the rate of valproate ion absorption may vary with the formulation administered (liquid, solid, or sprinkle), conditions of use (e.g., fasting or postprandial) and the method of administration (e.g., whether the contents of the capsule are sprinkled on food or the capsule is taken intact), these differences should be of minor clinical importance under the steady state conditions achieved in chronic use in the treatment of epilepsy.

However, it is possible that differences among the various valproate products in Tmax and Cmax could be important upon initiation of treatment. For example, in single dose studies, the effect of feeding had a greater influence on the rate of absorption of the tablet (increase in Tmax from 4 to 8 hours) than on the absorption of the sprinkle capsules (increase in Tmax from 3.3 to 4.8 hours).

While the absorption rate from the G.I. tract and fluctuation in valproate plasma concentrations vary with dosing regimen and formulation, the efficacy of valproate as an anticonvulsant in chronic use is unlikely to be affected. Experience employing dosing regimens from once-a-day to four-times-a-day, as well as studies in primate epilepsy models involving constant rate infusion, indicate that total daily systemic bioavailability (extent of absorption) is the primary determinant of seizure control and that differences in the ratios of plasma peak to trough concentrations between valproate formulations are inconsequential from a practical clinical standpoint. Whether or not rate of absorption influences the efficacy of valproate as an antimanic or antimigraine agent is unknown.

Co-administration of oral valproate products with food and substitution among the various divalproex sodium delayed-release tablets and valproic acid formulations should cause no clinical problems in the management of patients with epilepsy (see DOSAGE AND ADMINISTRATION). Nonetheless, any changes in dosage administration, or the addition or discontinuance of concomitant drugs should ordinarily be accompanied by close monitoring of clinical status and valproate plasma concentrations.

DistributionProtein Binding

The plasma protein binding of valproate is concentration dependent and the free fraction increases from approximately 10% at 40 µg/mL to 18.5% at 130 µg/mL. Protein binding of valproate is reduced in the elderly, in patients with chronic hepatic diseases, in patients with renal impairment, and in the presence of other drugs (e.g., aspirin). Conversely, valproate may displace certain protein-bound drugs (e.g., phenytoin, carbamazepine, warfarin, and tolbutamide). (See PRECAUTIONS, Drug Interactions for more detailed information on the pharmacokinetic interactions of valproate with other drugs.)

CNS Distribution

Valproate concentrations in cerebrospinal fluid (CSF) approximate unbound concentrations in plasma (about 10% of total concentration).

Metabolism

Valproate is metabolized almost entirely by the liver. In adult patients on monotherapy, 30-50% of an administered dose appears in urine as a glucuronide conjugate. Mitochondrial β-oxidation is the other major metabolic pathway, typically accounting for over 40% of the dose. Usually, less than 15-20% of the dose is eliminated by other oxidative mechanisms. Less than 3% of an administered dose is excreted unchanged in urine.

The relationship between dose and total valproate concentration is nonlinear; concentration does not increase proportionally with the dose, but rather, increases to a lesser extent due to saturable plasma protein binding. The kinetics of unbound drug are linear.

Elimination

Mean plasma clearance and volume of distribution for total valproate are 0.56 L/hr/1.73 m2 and 11 L/1.73 m2, respectively. Mean plasma clearance and volume of distribution for free valproate are 4.6 L/hr/1.73 m2 and 92 L/1.73 m2. Mean terminal half-life for valproate monotherapy ranged from 9 to 16 hours following oral dosing regimens of 250 to 1000 mg.

The estimates cited apply primarily to patients who are not taking drugs that affect hepatic metabolizing enzyme systems. For example, patients taking enzyme-inducing antiepileptic drugs (carbamazepine, phenytoin, and phenobarbital) will clear valproate more rapidly. Because of these changes in valproate clearance, monitoring of antiepileptic concentrations should be intensified whenever concomitant antiepileptics are introduced or withdrawn.

Special PopulationsEffect of AgeNeonates

Children within the first two months of life have a markedly decreased ability to eliminate valproate compared to older children and adults. This is a result of reduced clearance (perhaps due to delay in development of glucuronosyltransferase and other enzyme systems involved in valproate elimination) as well as increased volume of distribution (in part due to decreased plasma protein binding). For example, in one study, the half-life in children under 10 days ranged from 10 to 67 hours compared to a range of 7 to 13 hours in children greater than 2 months.

Children

Pediatric patients (i.e., between 3 months and 10 years) have 50% higher clearances expressed on weight (i.e., mL/min/kg) than do adults. Over the age of 10 years, children have pharmacokinetic parameters that approximate those of adults.

Elderly

The capacity of elderly patients (age range: 68 to 89 years) to eliminate valproate has been shown to be reduced compared to younger adults (age range: 22 to 26). Intrinsic clearance is reduced by 39%; the free fraction is increased by 44%. Accordingly, the initial dosage should be reduced in the elderly. (See DOSAGE AND ADMINISTRATION.)

Effect of Gender

There are no differences in the body surface area adjusted unbound clearance between males and females (4.8 ± 0.17 and 4.7 ± 0.07 L/hr per 1.73 m2, respectively).

Effect of Race

The effects of race on the kinetics of valproate have not been studied.

Effect of DiseaseLiver Disease

(See BOXED WARNING, CONTRAINDICATIONS, and WARNINGS.) Liver disease impairs the capacity to eliminate valproate. In one study, the clearance of free valproate was decreased by 50% in 7 patients with cirrhosis and by 16% in 4 patients with acute hepatitis, compared with 6 healthy subjects. In that study, the half-life of valproate was increased from 12 to 18 hours. Liver disease is also associated with decreased albumin concentrations and larger unbound fractions (2 to 2.6 fold increase) of valproate. Accordingly, monitoring of total concentrations may be misleading since free concentrations may be substantially elevated in patients with hepatic disease whereas total concentrations may appear to be normal.

Renal Disease

A slight reduction (27%) in the unbound clearance of valproate has been reported in patients with renal failure (creatinine clearance < 10 mL/minute); however, hemodialysis typically reduces valproate concentrations by about 20%. Therefore, no dosage adjustment appears to be necessary in patients with renal failure. Protein binding in these patients is substantially reduced; thus, monitoring total concentrations may be misleading.

Plasma Levels and Clinical Effect

The relationship between plasma concentration and clinical response is not well documented. One contributing factor is the nonlinear, concentration dependent protein binding of valproate which affects the clearance of the drug. Thus, monitoring of total serum valproate cannot provide a reliable index of the bioactive valproate species.

For example, because the plasma protein binding of valproate is concentration dependent, the free fraction increases from approximately 10% at 40 µg/mL to 18.5% at 130 µg/mL. Higher than expected free fractions occur in the elderly, in hyperlipidemic patients, and in patients with hepatic and renal diseases.

Epilepsy

The therapeutic range in epilepsy is commonly considered to be 50 to 100 µg/mL of total valproate, although some patients may be controlled with lower or higher plasma concentrations.

Mania

In placebo-controlled clinical trials of acute mania, patients were dosed to clinical response with trough plasma concentrations between 50 and 125 µg/mL (see DOSAGE AND ADMINISTRATION).

Clinical TrialsMania

The effectiveness of divalproex sodium delayed-release tablets for the treatment of acute mania was demonstrated in two 3 week, placebo controlled, parallel group studies.

(1) Study 1: The first study enrolled adult patients who met DSM-III-R criteria for Bipolar Disorder and who were hospitalized for acute mania. In addition, they had a history of failing to respond to or not tolerating previous lithium carbonate treatment. Divalproex sodium delayed-release tablets were initiated at a dose of 250 mg tid and adjusted to achieve serum valproate concentrations in a range of 50-100 µg/mL by day 7. Mean divalproex sodium delayed-release tablets doses for completers in this study were 1118, 1525, and 2402 mg/day at Days 7, 14, and 21, respectively. Patients were assessed on the Young Mania Rating Scale (YMRS; score ranges from 0-60), an augmented Brief Psychiatric Rating Scale (BPRS-A), and the Global Assessment Scale (GAS). Baseline scores and change from baseline in the Week 3 endpoint (last-observation-carry-forward) analysis were as follows:

Study 1
YMRS Total Score
Group | Baseline * | BL to Wk 3 † | Difference ‡
Placebo | 28.8 | +0.2
Divalproex sodium delayed-release tablets | 28.5 | -9.5 | 9.7
BPRS-A Total Score
Group | Baseline * | BL to Wk 3 † | Difference ‡
Placebo | 76.2 | +1.8
Divalproex sodium delayed-release tablets | 76.4 | -17.0 | 18.8
GAS Score
Group | Baseline * | BL to Wk 3 † | Difference ‡
Placebo | 31.8 | 0.0
Divalproex sodium delayed-release tablets | 30.3 | +18.1 | 18.1
*Mean score at baseline †Change from baseline to Week 3 (LOCF) ‡Difference in change from baseline to Week 3 endpoint (LOCF) between divalproex sodium delayed-release tablets and placebo

Divalproex sodium delayed-release tablets were statistically significantly superior to placebo on all three measures of outcome.

(2) Study 2: The second study enrolled adult patients who met Research Diagnostic Criteria for manic disorder and who were hospitalized for acute mania. Divalproex sodium delayed-release tablets were initiated at a dose of 250 mg tid and adjusted within a dose range of 750-2500 mg/day to achieve serum valproate concentrations in a range of 40-150 µg/mL. Mean divalproex sodium delayed-release tablets doses for completers in this study were 1116, 1683, and 2006 mg/day at Days 7, 14, and 21, respectively. Study 2 also included a lithium group for which lithium doses for completers were 1312, 1869, and 1984 mg/day at Days 7, 14, and 21, respectively. Patients were assessed on the Manic Rating Scale (MRS; score ranges from 11 -63), and the primary outcome measures were the total MRS score, and scores for two subscales of the MRS, i.e., the Manic Syndrome Scale (MSS) and the Behavior and Ideation Scale (BIS). Baseline scores and change from baseline in the Week 3 endpoint (last-observation-carry-forward) analysis were as follows:

Study 2
MRS Total Score
Group | Baseline * | BL to Day 21 † | Difference ‡
Placebo | 38.9 | -4.4
Lithium | 37.9 | -10.5 | 6.1
Divalproex sodium delayed-release tablets | 38.1 | -9.5 | 5.1
MSS Total Score
Group | Baseline * | BL to Day 21 † | Difference ‡
Placebo | 18.9 | -2.5
Lithium | 18.5 | -6.2 | 3.7
Divalproex sodium delayed-release tablets | 18.9 | -6.0 | 3.5
BIS Total Score
Group | Baseline * | BL to Day 21 † | Difference ‡
Placebo | 16.4 | -1.4
Lithium | 16.0 | -3.8 | 2.4
Divalproex sodium delayed-release tablets | 15.7 | -3.2 | 1.8
*Mean score at baseline †Change from baseline to Day 21 (LOCF) ‡Difference in change from baseline to Day 21 endpoint (LOCF) between divalproex sodium delayed-release tablets and placebo and lithium and placebo

Divalproex sodium delayed-release tablets were statistically significantly superior to placebo on all three measures of outcome. An exploratory analysis for age and gender effects on outcome did not suggest any differential responsiveness on the basis of age or gender.

A comparison of the percentage of patients showing ≥ 30% reduction in the symptom score from baseline in each treatment group, separated by study, is shown in Figure 1.

Figure 1: Percentage of Patients Achieving ≥ 30% Reduction in Symptom Score From Baseline

Migraine

The results of two multicenter, randomized, double-blind, placebo-controlled clinical trials established the effectiveness of divalproex sodium delayed-release tablets in the prophylactic treatment of migraine headache.

Both studies employed essentially identical designs and recruited patients with a history of migraine with or without aura (of at least 6 months in duration) who were experiencing at least 2 migraine headaches a month during the 3 months prior to enrollment. Patients with cluster headaches were excluded. Women of childbearing potential were excluded entirely from one study, but were permitted in the other if they were deemed to be practicing an effective method of contraception.

In each study following a 4 week single-blind placebo baseline period, patients were randomized, under double blind conditions, to divalproex sodium delayed-release tablets or placebo for a 12 week treatment phase, comprised of a 4 week dose titration period followed by an 8 week maintenance period. Treatment outcome was assessed on the basis of 4 week migraine headache rates during the treatment phase.

In the first study, a total of 107 patients (24 M, 83 F), ranging in age from 26 to 73 were randomized 2:1, divalproex sodium delayed-release tablets to placebo. Ninety patients completed the 8 week maintenance period. Drug dose titration, using 250 mg tablets, was individualized at the investigator's discretion. Adjustments were guided by actual/sham trough total serum valproate levels in order to maintain the study blind. In patients on divalproex sodium delayed-release tablets doses ranged from 500 to 2500 mg a day. Doses over 500 mg were given in three divided doses (TID). The mean dose during the treatment phase was 1087 mg/day resulting in a mean trough total valproate level of 72.5 µg/mL, with a range of 31 to 133 µg/mL.

The mean 4 week migraine headache rate during the treatment phase was 5.7 in the placebo group compared to 3.5 in the divalproex sodium delayed-release tablets group (see Figure 2). These rates were significantly different.

In the second study, a total of 176 patients (19 males and 157 females), ranging in age from 17 to 76 years, were randomized equally to one of three divalproex sodium delayed-release tablets dose groups (500, 1000, or 1500 mg/day) or placebo. The treatments were given in two divided doses (BID). One hundred thirty-seven patients completed the 8 week maintenance period. Efficacy was to be determined by a comparison of the 4 week migraine headache rate in the combined 1000/1500 mg/day group and placebo group.

The initial dose was 250 mg daily. The regimen was advanced by 250 mg every 4 days (8 days for 500 mg/day group), until the randomized dose was achieved. The mean trough total valproate levels during the treatment phase were 39.6, 62.5, and 72.5 µg/mL in the divalproex sodium delayed-release tablets 500, 1000, and 1500 mg/day groups, respectively.

The mean 4 week migraine headache rates during the treatment phase, adjusted for differences in baseline rates, were 4.5 in the placebo group, compared to 3.3, 3.0, and 3.3 in the divalproex sodium delayed-release tablets 500, 1000, and 1500 mg/day groups, respectively, based on intent-to-treat results (see Figure 2). Migraine headache rates in the combined divalproex sodium delayed-release tablets 1000/1500 mg group were significantly lower than in the placebo group.

Figure 2: Mean 4 Week Migraine Rates

Epilepsy

The efficacy of divalproex sodium delayed-release tablets in reducing the incidence of complex partial seizures (CPS) that occur in isolation or in association with other seizure types was established in two controlled trials.

In one, multiclinic, placebo controlled study employing an add-on design, (adjunctive therapy) 144 patients who continued to suffer eight or more CPS per 8 weeks during an 8 week period of monotherapy with doses of either carbamazepine or phenytoin sufficient to assure plasma concentrations within the "therapeutic range" were randomized to receive, in addition to their original antiepilepsy drug (AED), either divalproex sodium delayed-release tablets or placebo. Randomized patients were to be followed for a total of 16 weeks. The following table presents the findings.

Adjunctive Therapy Study Median Incidence of CPS per 8 Weeks
Add-on Treatment | Number of Patients | Baseline Incidence | Experimental Incidence
Divalproex sodium delayed-release tablets | 75 | 16.0 | 8.9 *
Placebo | 69 | 14.5 | 11.5
*Reduction from baseline statistically significantly greater for divalproex sodium delayed-release tablets than placebo at p ≤ 0.05 level.

Figure 3 presents the proportion of patients (X axis) whose percentage reduction from baseline in complex partial seizure rates was at least as great as that indicated on the Y axis in the adjunctive therapy study. A positive percent reduction indicates an improvement (i.e., a decrease in seizure frequency), while a negative percent reduction indicates worsening. Thus, in a display of this type, the curve for an effective treatment is shifted to the left of the curve for placebo. This figure shows that the proportion of patients achieving any particular level of improvement was consistently higher for divalproex sodium delayed-release tablets than for placebo. For example, 45% of patients treated with divalproex sodium delayed-release tablets had a ≥ 50% reduction in complex partial seizure rate compared to 23% of patients treated with placebo.

Figure 3

The second study assessed the capacity of divalproex sodium delayed-release tablets to reduce the incidence of CPS when administered as the sole AED. The study compared the incidence of CPS among patients randomized to either a high or low dose treatment arm. Patients qualified for entry into the randomized comparison phase of this study only if 1) they continued to experience 2 or more CPS per 4 weeks during an 8 to 12 week long period of monotherapy with adequate doses of an AED (i.e., phenytoin, carbamazepine, phenobarbital, or primidone) and 2) they made a successful transition over a two week interval to divalproex sodium delayed-release tablets. Patients entering the randomized phase were then brought to their assigned target dose, gradually tapered off their concomitant AED and followed for an interval as long as 22 weeks. Less than 50% of the patients randomized, however, completed the study. In patients converted to divalproex sodium delayed-release tablets monotherapy, the mean total valproate concentrations during monotherapy were 71 and 123 µg/mL in the low dose and high dose groups, respectively.

The following table presents the findings for all patients randomized who had at least one post-randomization assessment.

Monotherapy Study Median Incidence of CPS per 8 Weeks
Treatment | Number of Patients | Baseline Incidence | Randomized Phase Incidence
High dose divalproex sodium delayed-release tablets | 131 | 13.2 | 10.7 *
Low dose divalproex sodium delayed-release tablets | 134 | 14.2 | 13.8
*Reduction from baseline statistically significantly greater for high dose than low dose at p ≤ 0.05 level.

Figure 4 presents the proportion of patients (X axis) whose percentage reduction from baseline in complex partial seizure rates was at least as great as that indicated on the Y axis in the monotherapy study. A positive percent reduction indicates an improvement (i.e., a decrease in seizure frequency), while a negative percent reduction indicates worsening. Thus, in a display of this type, the curve for a more effective treatment is shifted to the left of the curve for a less effective treatment. This figure shows that the proportion of patients achieving any particular level of reduction was consistently higher for high dose divalproex sodium delayed-release tablets than for low dose divalproex sodium delayed-release tablets. For example, when switching from carbamazepine, phenytoin, phenobarbital or primidone monotherapy to high dose divalproex sodium delayed-release tablets monotherapy, 63% of patients experienced no change or a reduction in complex partial seizure rates compared to 54% of patients receiving low dose divalproex sodium delayed-release tablets.

Figure 4

INDICATIONS & USAGE SECTION

Mania

Divalproex sodium delayed-release tablets (divalproex sodium) are indicated for the treatment of the manic episodes associated with bipolar disorder. A manic episode is a distinct period of abnormally and persistently elevated, expansive, or irritable mood. Typical symptoms of mania include pressure of speech, motor hyperactivity, reduced need for sleep, flight of ideas, grandiosity, poor judgement, aggressiveness, and possible hostility.

The efficacy of divalproex sodium delayed-release tablets was established in 3 week trials with patients meeting DSM-III-R criteria for bipolar disorder who were hospitalized for acute mania (see Clinical Trials under CLINICAL PHARMACOLOGY).

The safety and effectiveness of divalproex sodium delayed-release tablets for long-term use in mania, i.e., more than 3 weeks, has not been systematically evaluated in controlled clinical trials. Therefore, healthcare providers who elect to use divalproex sodium delayed-release tablets for extended periods should continually reevaluate the long-term usefulness of the drug for the individual patient.

Epilepsy

Divalproex sodium delayed-release tablets (divalproex sodium) are indicated as monotherapy and adjunctive therapy in the treatment of patients with complex partial seizures that occur either in isolation or in association with other types of seizures. Divalproex sodium delayed-release tablets (divalproex sodium) are also indicated for use as sole and adjunctive therapy in the treatment of simple and complex absence seizures, and adjunctively in patients with multiple seizure types that include absence seizures.

Simple absence is defined as very brief clouding of the sensorium or loss of consciousness accompanied by certain generalized epileptic discharges without other detectable clinical signs. Complex absence is the term used when other signs are also present.

Migraine

Divalproex sodium delayed-release tablets are indicated for prophylaxis of migraine headaches. There is no evidence that divalproex sodium delayed-release tablets are useful in the acute treatment of migraine headaches. Because valproic acid may be a hazard to the fetus, divalproex sodium delayed-release tablets should be considered for women of childbearing potential only after this risk has been thoroughly discussed with the patient and weighed against the potential benefits of treatment (see WARNINGS, Usage In Pregnancy, PRECAUTIONS, Information for Patients).

SEE WARNINGS FOR STATEMENT REGARDING FATAL HEPATIC DYSFUNCTION.

CONTRAINDICATIONS SECTION

DIVALPROEX SODIUM SHOULD NOT BE ADMINISTERED TO PATIENTS WITH HEPATIC DISEASE OR SIGNIFICANT HEPATIC DYSFUNCTION.

Divalproex sodium is contraindicated in patients with known hypersensitivity to the drug.

Divalproex sodium is contraindicated in patients with known urea cycle disorders (see WARNINGS).

WARNINGS SECTION

Hepatotoxicity

Hepatic failure resulting in fatalities has occurred in patients receiving valproic acid. These incidents usually have occurred during the first six months of treatment. Serious or fatal hepatotoxicity may be preceded by non-specific symptoms such as malaise, weakness, lethargy, facial edema, anorexia, and vomiting. In patients with epilepsy, a loss of seizure control may also occur. Patients should be monitored closely for appearance of these symptoms. Liver function tests should be performed prior to therapy and at frequent intervals thereafter, especially during the first six months. However, healthcare providers should not rely totally on serum biochemistry since these tests may not be abnormal in all instances, but should also consider the results of careful interim medical history and physical examination.

Caution should be observed when administering divalproex sodium delayed-release tablets products to patients with a prior history of hepatic disease. Patients on multiple anticonvulsants, children, those with congenital metabolic disorders, those with severe seizure disorders accompanied by mental retardation, and those with organic brain disease may be at particular risk. Experience has indicated that children under the age of two years are at a considerably increased risk of developing fatal hepatotoxicity, especially those with the aforementioned conditions. When divalproex sodium delayed-release tablets are used in this patient group, it should be used with extreme caution and as a sole agent. The benefits of therapy should be weighed against the risks. Above this age group, experience in epilepsy has indicated that the incidence of fatal hepatotoxicity decreases considerably in progressively older patient groups.

The drug should be discontinued immediately in the presence of significant hepatic dysfunction, suspected or apparent. In some cases, hepatic dysfunction has progressed in spite of discontinuation of drug.

Pancreatitis

Cases of life-threatening pancreatitis have been reported in both children and adults receiving valproate. Some of the cases have been described as hemorrhagic with rapid progression from initial symptoms to death. Some cases have occurred shortly after initial use as well as after several years of use. The rate based upon the reported cases exceeds that expected in the general population and there have been cases in which pancreatitis recurred after rechallenge with valproate. In clinical trials, there were 2 cases of pancreatitis without alternative etiology in 2416 patients, representing 1044 patient-years experience. Patients and guardians should be warned that abdominal pain, nausea, vomiting, and/or anorexia can be symptoms of pancreatitis that require prompt medical evaluation. If pancreatitis is diagnosed, valproate should ordinarily be discontinued. Alternative treatment for the underlying medical condition should be initiated as clinically indicated (see BOXED WARNING).

Urea Cycle Disorders (UCD)

Divalproex sodium is contraindicated in patients with known urea cycle disorders. Hyperammonemic encephalopathy, sometimes fatal, has been reported following initiation of valproate therapy in patients with urea cycle disorders, a group of uncommon genetic abnormalities, particularly ornithine transcarbamylase deficiency. Prior to the initiation of valproate therapy, evaluation for UCD should be considered in the following patients: 1) those with a history of unexplained encephalopathy or coma, encephalopathy associated with a protein load, pregnancy-related or postpartum encephalopathy, unexplained mental retardation, or history of elevated plasma ammonia or glutamine; 2) those with cyclical vomiting and lethargy, episodic extreme irritability, ataxia, low BUN, or protein avoidance; 3) those with a family history of UCD or a family history of unexplained infant deaths (particularly males); 4) those with other signs or symptoms of UCD. Patients who develop symptoms of unexplained hyperammonemic encephalopathy while receiving valproate therapy should receive prompt treatment (including discontinuation of valproate therapy) and be evaluated for underlying urea cycle disorders (see CONTRAINDICATIONS and PRECAUTIONS).

Usage In Pregnancy

VALPROATE CAN PRODUCE TERATOGENIC EFFECTS. DATA SUGGEST THAT THERE IS AN INCREASED INCIDENCE OF CONGENITAL MALFORMATIONS ASSOCIATED WITH THE USE OF VALPROATE BY WOMEN WITH SEIZURE DISORDERS DURING PREGNANCY WHEN COMPARED TO THE INCIDENCE IN WOMEN WITH SEIZURE DISORDERS WHO DO NOT USE ANTIEPILEPTIC DRUGS DURING PREGNANCY, THE INCIDENCE IN WOMEN WITH SEIZURE DISORDERS WHO USE OTHER ANTIEPILEPTIC DRUGS, AND THE BACKGROUND INCIDENCE FOR THE GENERAL POPULATION. THEREFORE, VALPROATE SHOULD BE CONSIDERED FOR WOMEN OF CHILDBEARING POTENTIAL ONLY AFTER THE RISKS HAVE BEEN THOROUGHLY DISCUSSED WITH THE PATIENT AND WEIGHED AGAINST THE POTENTIAL BENEFITS OF TREATMENT.

THERE ARE MULTIPLE REPORTS IN THE CLINICAL LITERATURE THAT INDICATE THE USE OF ANTIEPILEPTIC DRUGS DURING PREGNANCY RESULTS IN AN INCREASED INCIDENCE OF CONGENITAL MALFORMATIONS IN OFFSPRING. ANTIEPILEPTIC DRUGS, INCLUDING VALPROATE, SHOULD BE ADMINISTERED TO WOMEN OF CHILDBEARING POTENTIAL ONLY IF THEY ARE CLEARLY SHOWN TO BE ESSENTIAL IN THE MANAGEMENT OF THEIR MEDICAL CONDITION.

Antiepileptic drugs should not be discontinued abruptly in patients in whom the drug is administered to prevent major seizures because of the strong possibility of precipitating status epilepticus with attendant hypoxia and threat to life. In individual cases where the severity and frequency of the seizure disorder are such that the removal of medication does not pose a serious threat to the patient, discontinuation of the drug may be considered prior to and during pregnancy, although it cannot be said with any confidence that even minor seizures do not pose some hazard to the developing embryo or fetus.

Human DataCongenital Malformations

The North American Antiepileptic Drug Pregnancy Registry reported 16 cases of congenital malformations among the offspring of 149 women with epilepsy who were exposed to valproic acid monotherapy during the first trimester of pregnancy at doses of approximately 1,000 mg per day, for a prevalence rate of 10.7% (95% CI 6.3%-16.9%). Three of the 149 offspring (2%) had neural tube defects and 6 of the 149 (4%) had less severe malformations. Among epileptic women who were exposed to other antiepileptic drug monotherapies during pregnancy (1,048 patients) the malformation rate was 2.9% (95% CI 2.0% to 4.1%). There was a 4 fold increase in congenital malformations among infants with valproic acid-exposed mothers compared with those treated with other antiepileptic monotherapies as a group (Odds Ratio 4.0; 95% CI 2.1 to 7.4). This increased risk does not reflect a comparison versus any specific antiepileptic drug, but the risk versus the heterogeneous group of all other antiepileptic drug monotherapies combined. The increased teratogenic risk from valproic acid in women with epilepsy is expected to be reflected in an increased risk in other indications (e.g., migraine or bipolar disorder).

THE STRONGEST ASSOCIATION OF MATERNAL VALPROATE USAGE WITH CONGENITAL MALFORMATIONS IS WITH NEURAL TUBE DEFECTS (AS DISCUSSED UNDER THE NEXT SUBHEADING). HOWEVER, OTHER CONGENITAL ANOMALIES (E.G., CRANIOFACIAL DEFECTS, CARDIOVASCULAR MALFORMATIONS AND ANOMALIES INVOLVING VARIOUS BODY SYSTEMS), COMPATIBLE AND INCOMPATIBLE WITH LIFE, HAVE BEEN REPORTED. SUFFICIENT DATA TO DETERMINE THE INCIDENCE OF THESE CONGENITAL ANOMALIES IS NOT AVAILABLE.

Neural Tube Defects

THE INCIDENCE OF NEURAL TUBE DEFECTS IN THE FETUS IS INCREASED IN MOTHERS RECEIVING VALPROATE DURING THE FIRST TRIMESTER OF PREGNANCY. THE CENTERS FOR DISEASE CONTROL (CDC) HAS ESTIMATED THE RISK OF VALPROIC ACID EXPOSED WOMEN HAVING CHILDREN WITH SPINA BIFIDA TO BE APPROXIMATELY 1 TO 2%. THE AMERICAN COLLEGE OF OBSTETRICIANS AND GYNECOLOGISTS (ACOG) ESTIMATES THE GENERAL POPULATION RISK FOR CONGENITAL NEURAL TUBE DEFECTS AS 0.14% TO 0.2%.

Tests to detect neural tube and other defects using current accepted procedures should be considered a part of routine prenatal care in pregnant women receiving valproate.

Evidence suggests that pregnant women who receive folic acid supplementation may be at decreased risk for congenital neural tube defects in their offspring compared to pregnant women not receiving folic acid. Whether the risk of neural tube defects in the offspring of women receiving valproate specifically is reduced by folic acid supplementation is unknown. DIETARY FOLIC ACID SUPPLEMENTATION BOTH PRIOR TO AND DURING PREGNANCY SHOULD BE ROUTINELY RECOMMENDED TO PATIENTS CONTEMPLATING PREGNANCY.

Other Adverse Pregnancy Effects

PATIENTS TAKING VALPROATE MAY DEVELOP CLOTTING ABNORMALITIES (SEE PRECAUTIONS, GENERAL AND WARNINGS). A PATIENT WHO HAD LOW FIBRINOGEN WHEN TAKING MULTIPLE ANTICONVULSANTS INCLUDING VALPROATE GAVE BIRTH TO AN INFANT WITH AFIBRINOGENEMIA WHO SUBSEQUENTLY DIED OF HEMORRHAGE. IF VALPROATE IS USED IN PREGNANCY, THE CLOTTING PARAMETERS SHOULD BE MONITORED CAREFULLY.

PATIENTS TAKING VALPROATE MAY DEVELOP HEPATIC FAILURE (SEE WARNINGS, HEPATOTOXICITY AND BOX WARNING). FATAL HEPATIC FAILURES, IN A NEWBORN AND IN AN INFANT, HAVE BEEN REPORTED FOLLOWING THE MATERNAL USE OF VALPROATE DURING PREGNANCY.

Animal Data

Animal studies have demonstrated valproate-induced teratogenicity. Increased frequencies of malformations, as well as intrauterine growth retardation and death, have been observed in mice, rats, rabbits, and monkeys following prenatal exposure to valproate. Malformations of the skeletal system are the most common structural abnormalities produced in experimental animals, but neural tube closure defects have been seen in mice exposed to maternal plasma valproate concentrations exceeding 230 µg/mL (2.3 times the upper limit of the human therapeutic range) during susceptible periods of embryonic development. Administration of an oral dose of 200 mg/kg/day or greater (50% of the maximum human daily dose or greater on a mg/m2 basis) to pregnant rats during organogenesis produced malformations (skeletal, cardiac, and urogenital) and growth retardation in the offspring. These doses resulted in peak maternal plasma valproate levels of approximately 340 µg/mL or greater (3.4 times the upper limit of the human therapeutic range or greater). Behavioral deficits have been reported in the offspring of rats given a dose of 200 mg/kg/day throughout most of pregnancy. An oral dose of 350 mg/kg/day (approximately 2 times the maximum human daily dose on a mg/m2 basis) produced skeletal and visceral malformations in rabbits exposed during organogenesis. Skeletal malformations, growth retardation, and death were observed in rhesus monkeys following administration of an oral dose of 200 mg/kg/day (equal to the maximum human daily dose on a mg/m2 basis) during organogenesis. This dose resulted in peak maternal plasma valproate levels of approximately 280 µg/mL (2.8 times the upper limit of the human therapeutic range).

Suicidal Behavior and Ideation

Antiepileptic drugs (AEDs), including divalproex sodium, increase the risk of suicidal thoughts or behavior in patients taking these drugs for any indication. Patients treated with any AED for any indication should be monitored for the emergence or worsening of depression, suicidal thoughts or behavior, and/or any unusual changes in mood or behavior.

Pooled analyses of 199 placebo-controlled clinical trials (mono- and adjunctive therapy) of 11 different AEDs showed that patients randomized to one of the AEDs had approximately twice the risk (adjusted Relative Risk 1.8, 95% CI:1.2, 2.7) of suicidal thinking or behavior compared to patients randomized to placebo. In these trials, which had a median treatment duration of 12 weeks, the estimated incidence rate of suicidal behavior or ideation among 27,863 AED-treated patients was 0.43%, compared to 0.24% among 16,029 placebo-treated patients, representing an increase of approximately one case of suicidal thinking or behavior for every 530 patients treated. There were four suicides in drug-treated patients in the trials and none in placebo-treated patients, but the number is too small to allow any conclusion about drug effect on suicide.

The increased risk of suicidal thoughts or behavior with AEDs was observed as early as one week after starting drug treatment with AEDs and persisted for the duration of treatment assessed. Because most trials included in the analysis did not extend beyond 24 weeks, the risk of suicidal thoughts or behavior beyond 24 weeks could not be assessed.

The risk of suicidal thoughts or behavior was generally consistent among drugs in the data analyzed. The finding of increased risk with AEDs of varying mechanisms of action and across a range of indications suggests that the risk applies to all AEDs used for any indication. The risk did not vary substantially by age (5-100 years) in the clinical trials analyzed.

Table 1 shows absolute and relative risk by indication for all evaluated AEDs.

Table 1. Risk by indication for antiepileptic drugs in the pooled analysis
Indication | Placebo Patients with Events Per 1000 Patients | Drug Patients with Events Per 1000 Patients | Relative Risk: Incidence of Events in Drug Patients/Incidence in Placebo Patients | Risk Difference: Additional Drug Patients with Events Per 1000 Patients
Epilepsy | 1.0 | 3.4 | 3.5 | 2.4
Psychiatric | 5.7 | 8.5 | 1.5 | 2.9
Other | 1.0 | 1.8 | 1.9 | 0.9
Total | 2.4 | 4.3 | 1.8 | 1.9

The relative risk for suicidal thoughts or behavior was higher in clinical trials for epilepsy than in clinical trials for psychiatric or other conditions, but the absolute risk differences were similar for the epilepsy and psychiatric indications.

Anyone considering prescribing divalproex sodium or any other AED must balance the risk of suicidal thoughts or behavior with the risk of untreated illness. Epilepsy and many other illnesses for which AEDs are prescribed are themselves associated with morbidity and mortality and an increased risk of suicidal thoughts and behavior. Should suicidal thoughts and behavior emerge during treatment, the prescriber needs to consider whether the emergence of these symptoms in any given patient may be related to the illness being treated.

Patients, their caregivers, and families should be informed that AEDs increase the risk of suicidal thoughts and behavior and should be advised of the need to be alert for the emergence or worsening of the signs and symptoms of depression, any unusual changes in mood or behavior, or the emergence of suicidal thoughts, behavior, or thoughts about self-harm. Behaviors of concern should be reported immediately to healthcare providers.

Interaction with Carbapenem Antibiotics

Carbapenem antibiotics (ertapenem, imipenem, meropenem) may reduce serum valproic acid concentrations to subtherapeutic levels, resulting in loss of seizure control. Serum valproic acid concentrations should be monitored frequently after initiating carbapenem therapy. Alternative antibacterial or anticonvulsant therapy should be considered if serum valproic acid concentrations drop significantly or seizure control deteriorates (see Drug Interactions).

Somnolence in the Elderly

In a double-blind, multicenter trial of valproate in elderly patients with dementia (mean age = 83 years), doses were increased by 125 mg/day to a target dose of 20 mg/kg/day. A significantly higher proportion of valproate patients had somnolence compared to placebo, and although not statistically significant, there was a higher proportion of patients with dehydration. Discontinuations for somnolence were also significantly higher than with placebo. In some patients with somnolence (approximately one-half), there was associated reduced nutritional intake and weight loss. There was a trend for the patients who experienced these events to have a lower baseline albumin concentration, lower valproate clearance, and a higher BUN. In elderly patients, dosage should be increased more slowly and with regular monitoring for fluid and nutritional intake, dehydration, somnolence, and other adverse events. Dose reductions or discontinuation of valproate should be considered in patients with decreased food or fluid intake and in patients with excessive somnolence (see DOSAGE AND ADMINISTRATION).

Thrombocytopenia

The frequency of adverse effects (particularly elevated liver enzymes and thrombocytopenia (see PRECAUTIONS) may be dose-related. In a clinical trial of divalproex sodium delayed-release tablets as monotherapy in patients with epilepsy, 34/126 patients (27%) receiving approximately 50 mg/kg/day on average, had at least one value of platelets ≤ 75 x 109/L. Approximately half of these patients had treatment discontinued, with return of platelet counts to normal. In the remaining patients, platelet counts normalized with continued treatment. In this study, the probability of thrombocytopenia appeared to increase significantly at total valproate concentrations of ≥ 110 µg/mL (females) or ≥ 135 µg/mL (males). The therapeutic benefit which may accompany the higher doses should therefore be weighed against the possibility of a greater incidence of adverse effects.

PRECAUTIONS SECTION

Hepatic Dysfunction

See BOXED WARNING, CONTRAINDICATIONS and WARNINGS.

Pancreatitis

See BOXED WARNING and WARNINGS.

Hypothermia

Hypothermia, defined as an unintentional drop in body core temperature to < 35° C (95° F), has been reported in association with valproate therapy both in conjunction with and in the absence of hyperammonemia. This adverse reaction can also occur in patients using concomitant topiramate with valproate after starting topiramate treatment or after increasing the daily dose of topiramate (see Drug Interactions- Topiramate). Consideration should be given to stopping valproate in patients who develop hypothermia, which may be manifested by a variety of clinical abnormalities including lethargy, confusion, coma, and significant alterations in other major organ systems such as the cardiovascular and respiratory systems. Clinical management and assessment should include examination of blood ammonia levels.

Hyperammonemia

Hyperammonemia has been reported in association with valproate therapy and may be present despite normal liver function tests. In patients who develop unexplained lethargy and vomiting or changes in mental status, hyperammonemic encephalopathy should be considered and an ammonia level should be measured.Hyperammonemia should also be considered in patients who present with hypothermia (see PRECAUTIONS, Hypothermia). If ammonia is increased, valproate therapy should be discontinued. Appropriate interventions for treatment of hyperammonemia should be initiated, and such patients should undergo investigation for underlying urea cycle disorders. (See CONTRAINDICATIONS and WARNINGS, Urea Cycle Disorders (UCD) and PRECAUTIONS, Hyperammonemia and Encephalopathy Associated with Concomitant Topiramate Use .)

Asymptomatic elevations of ammonia are more common and when present, require close monitoring of plasma ammonia levels. If the elevation persists, discontinuation of valproate therapy should be considered. In patients who develop unexplained lethargy, vomiting, or changes in mental status, hyperammonemic encephalopathy should be considered and an ammonia level should be measured. (See CONTRAINDICATIONS and WARNINGS, Urea Cycle Disorders and PRECAUTIONS, Hyperammonemia.)

Hyperammonemia and Encephalopathy Associated with Concomitant Topiramate Use

Concomitant administration of topiramate and valproic acid has been associated with hyperammonemia with or without encephalopathy in patients who have tolerated either drug alone. Clinical symptoms of hyperammonemic encephalopathy often include acute alterations in level of consciousness and/or cognitive function with lethargy or vomiting. Hypothermia can also be a manifestation of hyperammonemia (see PRECAUTIONS – Hypothermia). In most cases, symptoms and signs abated with discontinuation of either drug. This adverse event is not due to a pharmacokinetic interaction. It is not known if topiramate monotherapy is associated with hyperammonemia. Patients with inborn errors of metabolism or reduced hepatic mitochondrial activity may be at an increased risk for hyperammonemia with or without encephalopathy. Although not studied, an interaction of topiramate and valproic acid may exacerbate existing defects or unmask deficiencies in susceptible persons. In patients who develop unexplained lethargy, vomiting, or changes in mental status, hyperammonemic encephalopathy should be considered and an ammonia level should be measured. (See CONTRAINDICATIONS and WARNINGS, Urea Cycle Disorders; and PRECAUTIONS, Hyperammonemia.)

General

Because of reports of thrombocytopenia (see WARNINGS), inhibition of the secondary phase of platelet aggregation, and abnormal coagulation parameters, (e.g., low fibrinogen), platelet counts and coagulation tests are recommended before initiating therapy and at periodic intervals. It is recommended that patients receiving divalproex sodium delayed-release tablets be monitored for platelet count and coagulation parameters prior to planned surgery. In a clinical trial of divalproex sodium delayed-release tablets as monotherapy in patients with epilepsy, 34/126 patients (27%) receiving approximately 50 mg/kg/day on average, had at least one value of platelets ≤ 75 x 109/L. Approximately half of these patients had treatment discontinued, with return of platelet counts to normal. In the remaining patients, platelet counts normalized with continued treatment. In this study, the probability of thrombocytopenia appeared to increase significantly at total valproate concentrations of ≥ 110 µg/mL (females) or ≥ 135 µg/mL (males). Evidence of hemorrhage, bruising, or a disorder of hemostasis/coagulation is an indication for reduction of the dosage or withdrawal of therapy.

Since divalproex sodium delayed-release tablets may interact with concurrently administered drugs which are capable of enzyme induction, periodic plasma concentration determinations of valproate and concomitant drugs are recommended during the early course of therapy. (See PRECAUTIONS, Drug Interactions.)

Valproate is partially eliminated in the urine as a keto-metabolite which may lead to a false interpretation of the urine ketone test.

There have been reports of altered thyroid function tests associated with valproate. The clinical significance of these is unknown.

Suicidal ideation may be a manifestation of certain psychiatric disorders, and may persist until significant remission of symptoms occurs. Close supervision of high risk patients should accompany initial drug therapy.

There are in vitro studies that suggest valproate stimulates the replication of the HIV and CMV viruses under certain experimental conditions. The clinical consequence, if any, is not known. Additionally, the relevance of these in vitro findings is uncertain for patients receiving maximally suppressive antiretroviral therapy. Nevertheless, these data should be borne in mind when interpreting the results from regular monitoring of the viral load in HIV infected patients receiving valproate or when following CMV infected patients clinically.

Multi-organ Hypersensitivity Reaction

Multi-organ hypersensitivity reactions have been rarely reported in close temporal association to the initiation of valproate therapy in adult and pediatric patients (median time to detection 21 days: range 1 to 40 days). Although there have been a limited number of reports, many of these cases resulted in hospitalization and at least one death has been reported. Signs and symptoms of this disorder were diverse; however, patients typically, although not exclusively, presented with fever and rash associated with other organ system involvement. Other associated manifestations may include lymphadenopathy, hepatitis, liver function test abnormalities, hematological abnormalities (e.g., eosinophilia, thrombocytopenia, neutropenia), pruritis, nephritis, oliguria, hepato-renal syndrome, arthralgia, and asthenia. Because the disorder is variable in its expression, other organ system symptoms and signs, not noted here, may occur. If this reaction is suspected, valproate should be discontinued and an alternative treatment started. Although the existence of cross sensitivity with other drugs that produce this syndrome is unclear, the experience amongst drugs associated with multi-organ hypersensitivity would indicate this to be a possibility.

Information for PatientsPancreatitis

Patients and guardians should be warned that abdominal pain, nausea, vomiting, and/or anorexia can be symptoms of pancreatitis and, therefore, require further medical evaluation promptly

Hyperammonemia

Patients should be informed of the signs and symptoms associated with hyperammonemic encephalopathy (see PRECAUTIONS, Hyperammonemia) and be told to inform the prescriber if any of these symptoms occur.

CNS Depression

Since divalproex sodium delayed-release tablets products may produce CNS depression, especially when combined with another CNS depressant (e.g., alcohol), patients should be advised not to engage in hazardous activities, such as driving an automobile or operating dangerous machinery, until it is known that they do not become drowsy from the drug.

Birth Defects

Since divalproex sodium delayed-release tablets have been associated with certain types of birth defects, female patients of child-bearing age considering the use of divalproex sodium delayed-release tablets should be advised of the risk and of alternative therapeutic options and to read the Patient Information Leaflet, which appears as the last section of the labeling. This is especially important when the treatment of a spontaneously reversible condition not ordinarily associated with permanent injury or risk of death (e.g., migraine) is considered.

Patients should be encouraged to enroll in the North American Antiepileptic Drug (NAAED) Pregnancy Registry if they become pregnant. This registry is collecting information about the safety of antiepileptic drugs during pregnancy. To enroll, patients can call the toll free number 1-888-233-2334 (see PRECAUTIONS - Pregnancy).

Suicidal Thinking and Behavior

Patients, their caregivers, and families should be counseled that AEDs, including divalproex sodium, may increase the risk of suicidal thoughts and behavior and should be advised of the need to be alert for the emergence or worsening of symptoms of depression, any unusual changes in mood or behavior, or the emergence of suicidal thoughts, behavior, or thoughts about self-harm. Behaviors of concern should be reported immediately to the healthcare providers (see WARNINGS).

Multi-organ Hypersensitivity Reaction

Patients should be instructed that a fever associated with other organ system involvement (rash, lymphadenopathy, etc.) may be drug-related and should be reported to the physician immediately (see PRECAUTIONS, Multi-organ Hypersensitivity Reaction).

Drug InteractionsEffects of Co-Administered Drugs on Valproate Clearance

Drugs that affect the level of expression of hepatic enzymes, particularly those that elevate levels of glucuronosyltransferases, may increase the clearance of valproate. For example, phenytoin, carbamazepine, and phenobarbital (or primidone) can double the clearance of valproate. Thus, patients on monotherapy will generally have longer half-lives and higher concentrations than patients receiving polytherapy with antiepilepsy drugs.

In contrast, drugs that are inhibitors of cytochrome P450 isozymes, e.g., antidepressants, may be expected to have little effect on valproate clearance because cytochrome P450 microsomal mediated oxidation is a relatively minor secondary metabolic pathway compared to glucuronidation and beta-oxidation.

Because of these changes in valproate clearance, monitoring of valproate and concomitant drug concentrations should be increased whenever enzyme inducing drugs are introduced or withdrawn.

The following list provides information about the potential for an influence of several commonly prescribed medications on valproate pharmacokinetics. The list is not exhaustive nor could it be, since new interactions are continuously being reported.

Drugs for Which a Potentially Important Interaction Has Been ObservedAspirin

A study involving the Co-administration of aspirin at antipyretic doses (11 to 16 mg/kg) with valproate to pediatric patients (n = 6) revealed a decrease in protein binding and an inhibition of metabolism of valproate. Valproate free fraction was increased 4 fold in the presence of aspirin compared to valproate alone. The β-oxidation pathway consisting of 2-E-valproic acid, 3-OH-valproic acid, and 3-keto valproic acid was decreased from 25% of total metabolites excreted on valproate alone to 8.3% in the presence of aspirin. Caution should be observed if valproate and aspirin are to be co-administered.

Felbamate

A study involving the co-administration of 1200 mg/day of felbamate with valproate to patients with epilepsy (n = 10) revealed an increase in mean valproate peak concentration by 35% (from 86 to 115 µg/mL) compared to valproate alone. Increasing the felbamate dose to 2400 mg/day increased the mean valproate peak concentration to 133 µg/mL (another 16% increase). A decrease in valproate dosage may be necessary when felbamate therapy is initiated.

Carbapenem Antibiotics

A clinically significant reduction in serum valproic acid concentration has been reported in patients receiving carbapenem antibiotics (ertapenem, imipenem, meropenem) and may result in loss of seizure control. The mechanism of this interaction is not well understood. Serum valproic acid concentrations should be monitored frequently after initiating carbapenem therapy. Alternative antibacterial or anticonvulsant therapy should be considered if serum valproic acid concentrations drop significantly or seizure control deteriorates (See WARNINGS).

Rifampin

A study involving the administration of a single dose of valproate (7 mg/kg) 36 hours after 5 nights of daily dosing with rifampin (600 mg) revealed a 40% increase in the oral clearance of valproate. Valproate dosage adjustment may be necessary when it is co-administered with rifampin.

Drugs for Which Either No Interaction or a Likely Clinically Unimportant Interaction Has Been ObservedAntacids

A study involving the co-administration of valproate 500 mg with commonly administered antacids (Maalox, Trisogel, and Titralac - 160 mEq doses) did not reveal any effect on the extent of absorption of valproate.

Chlorpromazine

A study involving the administration of 100 to 300 mg/day of chlorpromazine to schizophrenic patients already receiving valproate (200 mg BID) revealed a 15% increase in trough plasma levels of valproate.

Haloperidol

A study involving the administration of 6 to 10 mg/day of haloperidol to schizophrenic patients already receiving valproate (200 mg BID) revealed no significant changes in valproate trough plasma levels.

Cimetidine and Ranitidine

Cimetidine and ranitidine do not affect the clearance of valproate.

Effects of Valproate on Other Drugs

Valproate has been found to be a weak inhibitor of some P450 isozymes, epoxide hydrase, and glucuronosyltransferases.

The following list provides information about the potential for an influence of valproate co-administration on the pharmacokinetics or pharmacodynamics of several commonly prescribed medications. The list is not exhaustive, since new interactions are continuously being reported.

Drugs for Which a Potentially Important Valproate Interaction Has Been ObservedAmitriptyline/Nortriptyline

Administration of a single oral 50 mg dose of amitriptyline to 15 normal volunteers (10 males and 5 females) who received valproate (500 mg BID) resulted in a 21% decrease in plasma clearance of amitriptyline and a 34% decrease in the net clearance of nortriptyline. Rare postmarketing reports of concurrent use of valproate and amitriptyline resulting in an increased amitriptyline level have been received. Concurrent use of valproate and amitriptyline has rarely been associated with toxicity. Monitoring of amitriptyline levels should be considered for patients taking valproate concomitantly with amitriptyline. Consideration should be given to lowering the dose of amitriptyline/nortriptyline in the presence of valproate.

Carbamazepine/carbamazepine 10,11-Epoxide

Serum levels of carbamazepine (CBZ) decreased 17% while that of carbamazepine-10,11-epoxide (CBZ-E) increased by 45% upon co-administration of valproate and CBZ to epileptic patients.

Clonazepam

The concomitant use of valproic acid and clonazepam may induce absence status in patients with a history of absence type seizures.

Diazepam

Valproate displaces diazepam from its plasma albumin binding sites and inhibits its metabolism. Co-administration of valproate (1500 mg daily) increased the free fraction of diazepam (10 mg) by 90% in healthy volunteers (n = 6). Plasma clearance and volume of distribution for free diazepam were reduced by 25% and 20%, respectively, in the presence of valproate. The elimination half-life of diazepam remained unchanged upon addition of valproate.

Ethosuximide

Valproate inhibits the metabolism of ethosuximide. Administration of a single ethosuximide dose of 500 mg with valproate (800 to 1600 mg/day) to healthy volunteers (n = 6) was accompanied by a 25% increase in elimination half-life of ethosuximide and a 15% decrease in its total clearance as compared to ethosuximide alone. Patients receiving valproate and ethosuximide, especially along with other anticonvulsants, should be monitored for alterations in serum concentrations of both drugs.

Lamotrigine

In a steady-state study involving 10 healthy volunteers, the elimination half-life of lamotrigine increased from 26 to 70 hours with valproate co-administration (a 165% increase). The dose of lamotrigine should be reduced when co-administered with valproate. Serious skin reactions (such as Stevens-Johnson Syndrome and toxic epidermal necrolysis) have been reported with concomitant lamotrigine and valproate administration. See lamotrigine package insert for details on lamotrigine dosing with concomitant valproate administration.

Phenobarbital

Valproate was found to inhibit the metabolism of phenobarbital. Co-administration of valproate (250 mg BID for 14 days) with phenobarbital to normal subjects (n = 6) resulted in a 50% increase in half-life and a 30% decrease in plasma clearance of phenobarbital (60 mg single-dose). The fraction of phenobarbital dose excreted unchanged increased by 50% in presence of valproate.

There is evidence for severe CNS depression, with or without significant elevations of barbiturate or valproate serum concentrations. All patients receiving concomitant barbiturate therapy should be closely monitored for neurological toxicity. Serum barbiturate concentrations should be obtained, if possible, and the barbiturate dosage decreased, if appropriate.

Primidone, which is metabolized to a barbiturate, may be involved in a similar interaction with valproate.

Phenytoin

Valproate displaces phenytoin from its plasma albumin binding sites and inhibits its hepatic metabolism. Co-administration of valproate (400 mg TID) with phenytoin (250 mg) in normal volunteers (n = 7) was associated with a 60% increase in the free fraction of phenytoin. Total plasma clearance and apparent volume of distribution of phenytoin increased 30% in the presence of valproate. Both the clearance and apparent volume of distribution of free phenytoin were reduced by 25%.

In patients with epilepsy, there have been reports of breakthrough seizures occurring with the combination of valproate and phenytoin. The dosage of phenytoin should be adjusted as required by the clinical situation.

Tolbutamide

From in vitro experiments, the unbound fraction of tolbutamide was increased from 20% to 50% when added to plasma samples taken from patients treated with valproate. The clinical relevance of this displacement is unknown.

Topiramate

Concomitant administration of valproic acid and topiramate has been associated with hyperammonemia with and without encephalopathy (see CONTRAINDICATIONS and WARNINGS, Urea Cycle Disorders and PRECAUTIONS, Hyperammonemia and Encephalopathy Associated with Concomitant Topiramate Use). Concomitant administration of topiramate with valproic acid has also been associated with hypothermia in patients who have tolerated either drug alone. It may be prudent to examine blood ammonia levels in patients in whom the onset of hypothermia has been reported (see PRECAUTIONS – Hypothermia and Hyperammonemia.)

Warfarin

In an in vitro study, valproate increased the unbound fraction of warfarin by up to 32.6%. The therapeutic relevance of this is unknown; however, coagulation tests should be monitored if divalproex sodium delayed-release tablets therapy is instituted in patients taking anticoagulants.

Zidovudine

In six patients who were seropositive for HIV, the clearance of zidovudine (100 mg q8h) was decreased by 38% after administration of valproate (250 or 500 mg q8h); the half-life of zidovudine was unaffected.

Drugs for Which Either No Interaction or a Likely Clinically Unimportant Interaction Has Been ObservedAcetaminophen

Valproate had no effect on any of the pharmacokinetic parameters of acetaminophen when it was concurrently administered to three epileptic patients.

Clozapine

In psychotic patients (n = 11), no interaction was observed when valproate was co-administered with clozapine.

Lithium

Co-administration of valproate (500 mg BID) and lithium carbonate (300 mg TID) to normal male volunteers (n = 16) had no effect on the steady-state kinetics of lithium.

Lorazepam

Concomitant administration of valproate (500 mg BID) and lorazepam (1 mg BID) in normal male volunteers (n = 9) was accompanied by a 17% decrease in the plasma clearance of lorazepam.

Oral Contraceptive Steroids

Administration of a single-dose of ethinyloestradiol (50 µg)/levonorgestrel (250 µg) to 6 women on valproate (200 mg BID) therapy for 2 months did not reveal any pharmacokinetic interaction.

Carcinogenesis, Mutagenesis, Impairment of FertilityCarcinogenesis

Valproic acid was administered orally to Sprague Dawley rats and ICR (HA/ICR) mice at doses of 80 and 170 mg/kg/day (approximately 10 to 50% of the maximum human daily dose on a mg/m2 basis) for two years. A variety of neoplasms were observed in both species. The chief findings were a statistically significant increase in the incidence of subcutaneous fibrosarcomas in high dose male rats receiving valproic acid and a statistically significant dose-related trend for benign pulmonary adenomas in male mice receiving valproic acid. The significance of these findings for humans is unknown.

Mutagenesis

Valproate was not mutagenic in an in vitro bacterial assay (Ames test), did not produce dominant lethal effects in mice, and did not increase chromosome aberration frequency in an in vivo cytogenetic study in rats. Increased frequencies of sister chromatid exchange (SCE) have been reported in a study of epileptic children taking valproate, but this association was not observed in another study conducted in adults. There is some evidence that increased SCE frequencies may be associated with epilepsy. The biological significance of an increase in SCE frequency is not known.

Fertility

Chronic toxicity studies in juvenile and adult rats and dogs demonstrated reduced spermatogenesis and testicular atrophy at oral doses of 400 mg/kg/day or greater in rats (approximately equivalent to or greater than the maximum human daily dose on a mg/m2 basis) and 150 mg/kg/day or greater in dogs (approximately 1.4 times the maximum human daily dose or greater on a mg/m2 basis). Segment I fertility studies in rats have shown doses up to 350 mg/kg/day (approximately equal to the maximum human daily dose on a mg/m2 basis) for 60 days to have no effect on fertility. THE EFFECT OF VALPROATE ON TESTICULAR DEVELOPMENT AND ON SPERM PRODUCTION AND FERTILITY IN HUMANS IS UNKNOWN.

PregnancyPregnancy category D

See WARNINGS. To provide information regarding the effects of in utero exposure to divalproex sodium delayed-release tablets, healthcare providers are advised to recommend that pregnant patients taking divalproex sodium delayed-release tablets enroll in the NAAED Pregnancy Registry. This can be done by calling the toll free number 1-888-233-2334, and must be done by patients themselves. Information on the registry can also be found at the website http://www.aedpregnancyregistry.org/.

Nursing Mothers

Valproate is excreted in breast milk. Concentrations in breast milk have been reported to be 1-10% of serum concentrations. It is not known what effect this would have on a nursing infant. Consideration should be given to discontinuing nursing when divalproex sodium is administered to a nursing woman.

Pediatric Use

Experience has indicated that pediatric patients under the age of two years are at a considerably increased risk of developing fatal hepatotoxicity, especially those with the aforementioned conditions (see BOXED WARNING). When divalproex sodium delayed-release tablets are used in this patient group, it should be used with extreme caution and as a sole agent. The benefits of therapy should be weighed against the risks. Above the age of 2 years, experience in epilepsy has indicated that the incidence of fatal hepatotoxicity decreases considerably in progressively older patient groups.

Younger children, especially those receiving enzyme-inducing drugs, will require larger maintenance doses to attain targeted total and unbound valproic acid concentrations.

The variability in free fraction limits the clinical usefulness of monitoring total serum valproic acid concentrations. Interpretation of valproic acid concentrations in children should include consideration of factors that affect hepatic metabolism and protein binding.

The safety and effectiveness of divalproex sodium delayed-release tablets for the treatment of acute mania has not been studied in individuals below the age of 18 years.

The safety and effectiveness of divalproex sodium delayed-release tablets for the prophylaxis of migraines has not been studied in individuals below the age of 16 years.

The basic toxicology and pathologic manifestations of valproate sodium in neonatal (4 day old) and juvenile (14 day old) rats are similar to those seen in young adult rats. However, additional findings, including renal alterations in juvenile rats and renal alterations and retinal dysplasia in neonatal rats, have been reported. These findings occurred at 240 mg/kg/day, a dosage approximately equivalent to the human maximum recommended daily dose on a mg/m2 basis. They were not seen at 90 mg/kg, or 40% of the maximum human daily dose on a mg/m2 basis.

Geriatric Use

No patients above the age of 65 years were enrolled in double-blind prospective clinical trials of mania associated with bipolar illness. In a case review study of 583 patients, 72 patients (12%) were greater than 65 years of age. A higher percentage of patients above 65 years of age reported accidental injury, infection, pain, somnolence, and tremor. Discontinuation of valproate was occasionally associated with the latter two events. It is not clear whether these events indicate additional risk or whether they result from preexisting medical illness and concomitant medication use among these patients.

A study of elderly patients with dementia revealed drug related somnolence and discontinuation for somnolence (see WARNINGS, Somnolence in the Elderly). The starting dose should be reduced in these patients, and dosage reductions or discontinuation should be considered in patients with excessive somnolence (see DOSAGE AND ADMINISTRATION).

There is insufficient information available to discern the safety and effectiveness of divalproex sodium delayed-release tablets for the prophylaxis of migraines in patients over 65.

ADVERSE REACTIONS SECTION

Mania

The incidence of treatment-emergent events has been ascertained based on combined data from two placebo-controlled clinical trials of divalproex sodium delayed-release tablets in the treatment of manic episodes associated with bipolar disorder. The adverse events were usually mild or moderate in intensity, but sometimes were serious enough to interrupt treatment. In clinical trials, the rates of premature termination due to intolerance were not statistically different between placebo, divalproex sodium delayed-release tablets and lithium carbonate. A total of 4%, 8% and 11% of patients discontinued therapy due to intolerance in the placebo, divalproex sodium delayed-release tablets and lithium carbonate groups, respectively.

Table 2 summarizes those adverse events reported for patients in these trials where the incidence rate in the divalproex sodium delayed-release tablets-treated group was greater than 5% and greater than the placebo incidence, or where the incidence in the divalproex sodium delayed-release tablets-treated group was statistically significantly greater than the placebo group. Vomiting was the only event that was reported by significantly (p ≤ 0.05) more patients receiving divalproex sodium delayed-release tablets compared to placebo.

Table 2. Adverse Events Reported by > 5% of Divalproex Sodium Delayed-Release Tablets-Treated Patients During Placebo-Controlled Trials of Acute Mania *
Adverse Event | Divalproex Sodium Delayed-Release Tablets(n = 89) | Placebo (n = 97)
Nausea | 22% | 15%
Somnolence | 19% | 12%
Dizziness | 12% | 4%
Vomiting | 12% | 3%
Asthenia | 10% | 7%
Abdominal pain | 9% | 8%
Dyspepsia | 9% | 8%
Rash | 6% | 3%
*The following adverse events occurred at an equal or greater incidence for placebo than for divalproex sodium delayed-release tablets: back pain, headache, constipation, diarrhea, tremor, and pharyngitis.

The following additional adverse events were reported by greater than 1% but not more than 5% of the 89 divalproex sodium-treated patients in controlled clinical trials:

Body as a Whole

Chest pain, chills, chills and fever, fever, neck pain, neck rigidity.

Cardiovascular System

Hypertension, hypotension, palpitations, postural hypotension, tachycardia, vasodilation.

Digestive System

Anorexia, fecal incontinence, flatulence, gastroenteritis, glossitis, periodontal abscess.

Hemic and Lymphatic System

Ecchymosis.

Metabolic and Nutritional Disorders

Edema, peripheral edema.

Musculoskeletal System

Arthralgia, arthrosis, leg cramps, twitching.

Nervous System

Abnormal dreams, abnormal gait, agitation, ataxia, catatonic reaction, confusion, depression, diplopia, dysarthria, hallucinations, hypertonia, hypokinesia, insomnia, paresthesia, reflexes increased, tardive dyskinesia, thinking abnormalities, vertigo.

Respiratory System

Dyspnea, rhinitis.

Skin and Appendages

Alopecia, discoid lupus erythematosis, dry skin, furunculosis, maculopapular rash, seborrhea.

Special Senses

Amblyopia, conjunctivitis, deafness, dry eyes, ear pain, eye pain, tinnitus.

Urogenital System

Dysmenorrhea, dysuria, urinary incontinence.

Migraine

Based on two placebo-controlled clinical trials and their long term extension, divalproex sodium delayed-release tablets were generally well tolerated with most adverse events rated as mild to moderate in severity. Of the 202 patients exposed to divalproex sodium delayed-release tablets in the placebo-controlled trials, 17% discontinued for intolerance. This is compared to a rate of 5% for the 81 placebo patients. Including the long term extension study, the adverse events reported as the primary reason for discontinuation by ≥ 1% of 248 divalproex sodium delayed-release tablets-treated patients were alopecia (6%), nausea and/or vomiting (5%), weight gain (2%), tremor (2%), somnolence (1%), elevated SGOT and/or SGPT (1%), and depression (1%).

Table 3 includes those adverse events reported for patients in the placebo-controlled trials where the incidence rate in the divalproex sodium delayed-release tablets-treated group was greater than 5% and was greater than that for placebo patients.

Table 3. Adverse Events Reported by > 5% of Divalproex Sodium Delayed-Release Tablets-Treated Patients During Migraine Placebo-Controlled Trials with a Greater Incidence Than Patients Taking Placebo *
Body System Event | Divalproex Sodium Delayed-Release Tablets (N = 202) | Placebo (N = 81)
Gastrointestinal System
Nausea | 31% | 10%
Dyspepsia | 13% | 9%
Diarrhea | 12% | 7%
Vomiting | 11% | 1%
Abdominal pain | 9% | 4%
Increased appetite | 6% | 4%
Nervous System
Asthenia | 20% | 9%
Somnolence | 17% | 5%
Dizziness | 12% | 6%
Tremor | 9% | 0%
Other
Weight gain | 8% | 2%
Back pain | 8% | 6%
Alopecia | 7% | 1%
*The following adverse events occurred in at least 5% of divalproex sodium delayed-release tablets-treated patients and at an equal or greater incidence for placebo than for divalproex sodium delayed-release tablets: flu syndrome and pharyngitis.

The following additional adverse events were reported by greater than 1% but not more than 5% of the 202 divalproex sodium-treated patients in the controlled clinical trials:

Body as a Whole

Chest pain, chills, face edema, fever and malaise.

Cardiovascular System

Vasodilatation.

Digestive System

Anorexia, constipation, dry mouth, flatulence, gastrointestinal disorder (unspecified), and stomatitis.

Hemic and Lymphatic System

Ecchymosis.

Metabolic and Nutritional Disorders

Peripheral edema, SGOT increase, and SGPT increase.

Musculoskeletal System

Leg cramps and myalgia.

Nervous System

Abnormal dreams, amnesia, confusion, depression, emotional lability, insomnia, nervousness, paresthesia, speech disorder, thinking abnormalities, and vertigo.

Respiratory System

Cough increased, dyspnea, rhinitis, and sinusitis.

Skin and Appendages

Pruritus and rash.

Special Senses

Conjunctivitis, ear disorder, taste perversion, and tinnitus.

Urogenital System

Cystitis, metrorrhagia, and vaginal hemorrhage.

Epilepsy

Based on a placebo-controlled trial of adjunctive therapy for treatment of complex partial seizures, divalproex sodium delayed-release tablets were generally well tolerated with most adverse events rated as mild to moderate in severity. Intolerance was the primary reason for discontinuation in the divalproex sodium delayed-release tablets-treated patients (6%), compared to 1% of placebo-treated patients.

Table 4 lists treatment-emergent adverse events which were reported by ≥ 5% of divalproex sodium delayed-release tablets-treated patients and for which the incidence was greater than in the placebo group, in the placebo-controlled trial of adjunctive therapy for treatment of complex partial seizures. Since patients were also treated with other antiepilepsy drugs, it is not possible, in most cases, to determine whether the following adverse events can be ascribed to divalproex sodium delayed-release tablets alone, or the combination of divalproex sodium delayed-release tablets and other antiepilepsy drugs.

Table 4. Adverse Events Reported by ≥ 5% of Patients Treated with Divalproex Sodium Delayed-Release Tablets During Placebo-Controlled Trial of Adjunctive Therapy for Complex Partial Seizures
Body System/Event | Divalproex Sodium Delayed-Release Tablets (%) (n = 77) | Placebo (%) (n = 70)
Body as a Whole
Headache | 31 | 21
Asthenia | 27 | 7
Fever | 6 | 4
Gastrointestinal System
Nausea | 48 | 14
Vomiting | 27 | 7
Abdominal Pain | 23 | 6
Diarrhea | 13 | 6
Anorexia | 12 | 0
Dyspepsia | 8 | 4
Constipation | 5 | 1
Nervous System
Somnolence | 27 | 11
Tremor | 25 | 6
Dizziness | 25 | 13
Diplopia | 16 | 9
Amblyopia/Blurred Vision | 12 | 9
Ataxia | 8 | 1
Nystagmus | 8 | 1
Emotional Lability | 6 | 4
Thinking Abnormal | 6 | 0
Amnesia | 5 | 1
Respiratory System
Flu Syndrome | 12 | 9
Infection | 12 | 6
Bronchitis | 5 | 1
Rhinitis | 5 | 4
Other
Alopecia | 6 | 1
Weight Loss | 6 | 0

Table 5 lists treatment-emergent adverse events which were reported by ≥ 5% of patients in the high dose divalproex sodium delayed-release tablets group, and for which the incidence was greater than in the low dose group, in a controlled trial of divalproex sodium delayed-release tablets monotherapy treatment of complex partial seizures. Since patients were being titrated off another antiepilepsy drug during the first portion of the trial, it is not possible, in many cases, to determine whether the following adverse events can be ascribed to divalproex sodium delayed-release tablets alone, or the combination of divalproex sodium delayed-release tablets and other antiepilepsy drugs.

Table 5. Adverse Events Reported by ≥ 5% of Patients in the High Dose Group in the Controlled Trial of Divalproex Sodium Delayed-Release Tablets Monotherapy for Complex Partial Seizures *
Body System/Event | High Dose (%) (n = 131) | Low Dose (%) (n = 134)
Body as a Whole
Asthenia | 21 | 10
Digestive System
Nausea | 34 | 26
Diarrhea | 23 | 19
Vomiting | 23 | 15
Abdominal Pain | 12 | 9
Anorexia | 11 | 4
Dyspepsia | 11 | 10
Hemic/Lymphatic System
Thrombocytopenia | 24 | 1
Ecchymosis | 5 | 4
Metabolic/Nutritional
Weight Gain | 9 | 4
Peripheral Edema | 8 | 3
Nervous System
Tremor | 57 | 19
Somnolence | 30 | 18
Dizziness | 18 | 13
Insomnia | 15 | 9
Nervousness | 11 | 7
Amnesia | 7 | 4
Nystagmus | 7 | 1
Depression | 5 | 4
Respiratory System
Infection | 20 | 13
Pharyngitis | 8 | 2
Dyspnea | 5 | 1
Skin and Appendages
Alopecia | 24 | 13
Special Senses
Amblyopia/Blurred Vision | 8 | 4
Tinnitus | 7 | 1
*Headache was the only adverse event that occurred in ≥ 5% of patients in the high dose group and at an equal or greater incidence in the low dose group.

The following additional adverse events were reported by greater than 1% but less than 5% of the 358 patients treated with divalproex sodium delayed-release tablets in the controlled trials of complex partial seizures:

Body as a Whole

Back pain, chest pain, malaise.

Cardiovascular System

Tachycardia, hypertension, palpitation.

Digestive System

Increased appetite, flatulence, hematemesis, eructation, pancreatitis, periodontal abscess.

Hemic and Lymphatic System

Petechia.

Metabolic and Nutritional Disorders

SGOT increased, SGPT increased.

Musculoskeletal System

Myalgia, twitching, arthralgia, leg cramps, myasthenia.

Nervous System

Anxiety, confusion, abnormal gait, paresthesia, hypertonia, incoordination, abnormal dreams, personality disorder.

Respiratory System

Sinusitis, cough increased, pneumonia, epistaxis.

Skin and Appendages

Rash, pruritus, dry skin.

Special Senses

Taste perversion, abnormal vision, deafness, otitis media.

Urogenital System

Urinary incontinence, vaginitis, dysmenorrhea, amenorrhea, urinary frequency.

Other Patient Populations

Adverse events that have been reported with all dosage forms of valproate from epilepsy trials, spontaneous reports, and other sources are listed below by body system.

Gastrointestinal

The most commonly reported side effects at the initiation of therapy are nausea, vomiting, and indigestion. These effects are usually transient and rarely require discontinuation of therapy. Diarrhea, abdominal cramps, and constipation have been reported. Both anorexia with some weight loss and increased appetite with weight gain have also been reported. The administration of delayed-release divalproex sodium may result in reduction of gastrointestinal side effects in some patients.

CNS Effects

Sedative effects have occurred in patients receiving valproate alone but occur most often in patients receiving combination therapy. Sedation usually abates upon reduction of other antiepileptic medication. Tremor (may be dose-related), hallucinations, ataxia, headache, nystagmus, diplopia, asterixis, "spots before eyes", dysarthria, dizziness, confusion, hypesthesia, vertigo, incoordination, and parkinsonism have been reported with the use of valproate. Rare cases of coma have occurred in patients receiving valproate alone or in conjunction with phenobarbital. In rare instances encephalopathy with or without fever has developed shortly after the introduction of valproate monotherapy without evidence of hepatic dysfunction or inappropriately high plasma valproate levels. Although recovery has been described following drug withdrawal, there have been fatalities in patients with hyperammonemic encephalopathy, particularly in patients with underlying urea cycle disorders (see WARNINGS, Urea Cycle Disorders and PRECAUTIONS).

Several reports have noted reversible cerebral atrophy and dementia in association with valproate therapy.

Dermatologic

Transient hair loss, skin rash, photosensitivity, generalized pruritus, erythema multiforme, and Stevens-Johnson syndrome. Rare cases of toxic epidermal necrolysis have been reported including a fatal case in a 6-month-old infant taking valproate and several other concomitant medications. An additional case of toxic epidermal necrosis resulting in death was reported in a 35-year-old patient with AIDS taking several concomitant medications and with a history of multiple cutaneous drug reactions. Serious skin reactions have been reported with concomitant administration of lamotrigine and valproate (see PRECAUTIONS, Drug Interactions).

Psychiatric

Emotional upset, depression, psychosis, aggression, hyperactivity, hostility, and behavioral deterioration.

Musculoskeletal

Weakness.

Hematologic

Thrombocytopenia and inhibition of the secondary phase of platelet aggregation may be reflected in altered bleeding time, petechiae, bruising, hematoma formation, epistaxis, and frank hemorrhage (see PRECAUTIONS, General and Drug Interactions). Relative lymphocytosis, macrocytosis, hypofibrinogenemia, leukopenia, eosinophilia, anemia including macrocytic with or without folate deficiency, bone marrow suppression, pancytopenia, aplastic anemia, agranulocytosis, and acute intermittent porphyria.

Hepatic

Minor elevations of transaminases (e.g., SGOT and SGPT) and LDH are frequent and appear to be dose-related. Occasionally, laboratory test results include increases in serum bilirubin and abnormal changes in other liver function tests. These results may reflect potentially serious hepatotoxicity (see WARNINGS).

Endocrine

Irregular menses, secondary amenorrhea, breast enlargement, galactorrhea, and parotid gland swelling. Abnormal thyroid function tests (see PRECAUTIONS).

There have been rare spontaneous reports of polycystic ovary disease. A cause and effect relationship has not been established.

Pancreatic

Acute pancreatitis including fatalities (see WARNINGS).

Metabolic

Hyperammonemia (see PRECAUTIONS), hyponatremia, and inappropriate ADH secretion.

There have been rare reports of Fanconi's syndrome occurring chiefly in children.

Decreased carnitine concentrations have been reported although the clinical relevance is undetermined.

Hyperglycinemia has occurred and was associated with a fatal outcome in a patient with pre-existent nonketotic hyperglycinemia.

Genitourinary

Enuresis and urinary tract infection.

Special Senses

Hearing loss, either reversible or irreversible, has been reported; however, a cause and effect relationship has not been established. Ear pain has also been reported.

Other

Allergic reaction, anaphylaxis, edema of the extremities, lupus erythematosus, bone pain, cough increased, pneumonia, otitis media, bradycardia, cutaneous vasculitis, fever, and hypothermia.

OVERDOSAGE SECTION

Overdosage with valproate may result in somnolence, heart block, and deep coma. Fatalities have been reported; however patients have recovered from valproate levels as high as 2120 µg/mL.

In overdose situations, the fraction of drug not bound to protein is high and hemodialysis or tandem hemodialysis plus hemoperfusion may result in significant removal of drug. The benefit of gastric lavage or emesis will vary with the time since ingestion. General supportive measures should be applied with particular attention to the maintenance of adequate urinary output.

Naloxone has been reported to reverse the CNS depressant effects of valproate overdosage. Because naloxone could theoretically also reverse the antiepileptic effects of valproate, it should be used with caution in patients with epilepsy.

DOSAGE & ADMINISTRATION SECTION

Mania

Divalproex sodium delayed-release tablets are administered orally. The recommended initial dose is 750 mg daily in divided doses. The dose should be increased as rapidly as possible to achieve the lowest therapeutic dose which produces the desired clinical effect or the desired range of plasma concentrations. In placebo-controlled clinical trials of acute mania, patients were dosed to a clinical response with a trough plasma concentration between 50 and 125 µg/mL. Maximum concentrations were generally achieved within 14 days. The maximum recommended dosage is 60 mg/kg/day.

There is no body of evidence available from controlled trials to guide a clinician in the longer term management of a patient who improves during divalproex sodium delayed-release tablets treatment of an acute manic episode. While it is generally agreed that pharmacological treatment beyond an acute response in mania is desirable, both for maintenance of the initial response and for prevention of new manic episodes, there are no systematically obtained data to support the benefits of divalproex sodium delayed-release tablets in such longer-term treatment. Although there are no efficacy data that specifically address longer-term antimanic treatment with divalproex sodium delayed-release tablets, the safety of divalproex sodium delayed-release tablets in long-term use is supported by data from record reviews involving approximately 360 patients treated with divalproex sodium delayed-release tablets for greater than 3 months.

Epilepsy

Divalproex sodium delayed-release tablets are administered orally. Divalproex sodium delayed-release tablets are indicated as monotherapy and adjunctive therapy in complex partial seizures in adults and pediatric patients down to the age of 10 years, and in simple and complex absence seizures. As the divalproex sodium delayed-release tablets dosage is titrated upward, concentrations of phenobarbital, carbamazepine, and/or phenytoin may be affected (see PRECAUTIONS, Drug Interactions).

Complex Partial Seizures

For adults and children 10 years of age or older.

Monotherapy (Initial Therapy)

Divalproex sodium delayed-release tablets have not been systematically studied as initial therapy. Patients should initiate therapy at 10 to 15 mg/kg/day. The dosage should be increased by 5 to 10 mg/kg/week to achieve optimal clinical response. Ordinarily, optimal clinical response is achieved at daily doses below 60 mg/kg/day. If satisfactory clinical response has not been achieved, plasma levels should be measured to determine whether or not they are in the usually accepted therapeutic range (50 to 100 µg/mL). No recommendation regarding the safety of valproate for use at doses above 60 mg/kg/day can be made.

The probability of thrombocytopenia increases significantly at total trough valproate plasma concentrations above 110 µg/mL in females and 135 µg/mL in males. The benefit of improved seizure control with higher doses should be weighed against the possibility of a greater incidence of adverse reactions.

Conversion to Monotherapy

Patients should initiate therapy at 10 to 15 mg/kg/day. The dosage should be increased by 5 to 10 mg/kg/week to achieve optimal clinical response. Ordinarily, optimal clinical response is achieved at daily doses below 60 mg/kg/day. If satisfactory clinical response has not been achieved, plasma levels should be measured to determine whether or not they are in the usually accepted therapeutic range (50-100 µg/mL). No recommendation regarding the safety of valproate for use at doses above 60 mg/kg/day can be made. Concomitant antiepilepsy drug (AED) dosage can ordinarily be reduced by approximately 25% every 2 weeks. This reduction may be started at initiation of divalproex sodium delayed-release tablets therapy, or delayed by 1 to 2 weeks if there is a concern that seizures are likely to occur with a reduction. The speed and duration of withdrawal of the concomitant AED can be highly variable, and patients should be monitored closely during this period for increased seizure frequency.

Adjunctive Therapy

Divalproex sodium delayed-release tablets may be added to the patient's regimen at a dosage of 10 to 15 mg/kg/day. The dosage may be increased by 5 to 10 mg/kg/week to achieve optimal clinical response. Ordinarily, optimal clinical response is achieved at daily doses below 60 mg/kg/day. If satisfactory clinical response has not been achieved, plasma levels should be measured to determine whether or not they are in the usually accepted therapeutic range (50 to 100 µg/mL). No recommendation regarding the safety of valproate for use at doses above 60 mg/kg/day can be made. If the total daily dose exceeds 250 mg, it should be given in divided doses.

In a study of adjunctive therapy for complex partial seizures in which patients were receiving either carbamazepine or phenytoin in addition to divalproex sodium delayed-release tablets, no adjustment of carbamazepine or phenytoin dosage was needed (see CLINICAL STUDIES). However, since valproate may interact with these or other concurrently administered AEDs as well as other drugs (see Drug Interactions), periodic plasma concentration determinations of concomitant AEDs are recommended during the early course of therapy (see PRECAUTIONS, Drug Interactions).

Simple and Complex Absence Seizures

The recommended initial dose is 15 mg/kg/day, increasing at one week intervals by 5 to 10 mg/kg/day until seizures are controlled or side effects preclude further increases. The maximum recommended dosage is 60 mg/kg/day. If the total daily dose exceeds 250 mg, it should be given in divided doses.

A good correlation has not been established between daily dose, serum concentrations, and therapeutic effect. However, therapeutic valproate serum concentrations for most patients with absence seizures is considered to range from 50 to 100 µg/mL. Some patients may be controlled with lower or higher serum concentrations (see CLINICAL PHARMACOLOGY).

As the divalproex sodium delayed-release tablets dosage is titrated upward, blood concentrations of phenobarbital and/or phenytoin may be affected (see PRECAUTIONS).

Antiepilepsy drugs should not be abruptly discontinued in patients in whom the drug is administered to prevent major seizures because of the strong possibility of precipitating status epilepticus with attendant hypoxia and threat to life.

In epileptic patients previously receiving valproic acid therapy, divalproex sodium delayed-release tablets should be initiated at the same daily dose and dosing schedule. After the patient is stabilized on divalproex sodium delayed-release tablets, a dosing schedule of two or three times a day may be elected in selected patients.

Migraine

Divalproex sodium delayed-release tablets are administered orally. The recommended starting dose is 250 mg twice daily. Some patients may benefit from doses up to 1000 mg/day. In the clinical trials, there was no evidence that higher doses led to greater efficacy.

General Dosing AdviceDosing in Elderly Patients

Due to a decrease in unbound clearance of valproate and possibly a greater sensitivity to somnolence in the elderly, the starting dose should be reduced in these patients. Dosage should be increased more slowly and with regular monitoring for fluid and nutritional intake, dehydration, somnolence, and other adverse events. Dose reductions or discontinuation of valproate should be considered in patients with decreased food or fluid intake and in patients with excessive somnolence. The ultimate therapeutic dose should be achieved on the basis of both tolerability and clinical response (see WARNINGS).

Dose-Related Adverse Events

The frequency of adverse effects (particularly elevated liver enzymes and thrombocytopenia) may be dose-related. The probability of thrombocytopenia appears to increase significantly at total valproate concentrations of ≥ 110 µg/mL (females) or ≥ 135 µg/mL (males) (see PRECAUTIONS). The benefit of improved therapeutic effect with higher doses should be weighed against the possibility of a greater incidence of adverse reactions.

G.I. Irritation

Patients who experience G.I. irritation may benefit from administration of the drug with food or by slowly building up the dose from an initial low level.

HOW SUPPLIED SECTION

Divalproex sodium delayed-release tablets USP are supplied as:

The 125 mg tablets are pink colored, oval shaped, biconvex coated tablets imprinted ‘796’ with black ink on one side and plain on the other side.

Bottles of 30’s with Child Resistant Cap…...............NDC 62756-796-83

Bottles of 100’s with Child Resistant Cap ……..… NDC 62756-796-88

Bottles of 100’s with Non Child Resistant Cap….....NDC 62756-796-08

Bottles of 500’s with Non Child Resistant Cap….....NDC 62756-796-13

Bottles of 1000’s with Non Child Resistant Cap…...NDC 62756-796-18

The 250 mg tablets are orange colored, oval shaped, biconvex coated tablets imprinted ‘797’ with black ink on one side and plain on the other side.

Bottles of 30’s with Child Resistant Cap…...............NDC 62756-797-83

Bottles of 100’s with Child Resistant Cap ……..… NDC 62756-797-88

Bottles of 100’s with Non Child Resistant Cap….....NDC 62756-797-08

Bottles of 500’s with Non Child Resistant Cap….....NDC 62756-797-13

Bottles of 1000’s with Non Child Resistant Cap…...NDC 62756-797-18

The 500 mg tablets are pink colored, oval shaped, biconvex coated tablets imprinted ‘798’ with black ink on one side and plain on the other side.

Bottles of 30’s with Child Resistant Cap…...............NDC 62756-798-83

Bottles of 100’s with Child Resistant Cap ……..… NDC 62756-798-88

Bottles of 100’s with Non Child Resistant Cap….....NDC 62756-798-08

Bottles of 500’s with Non Child Resistant Cap….....NDC 62756-798-13

Bottles of 1000’s with Non Child Resistant Cap…...NDC 62756-798-18

Recommended storage: Store at 20° - 25°C (68° - 77°F); excursions permitted to 15° - 30° C (59° - 86° F) [see USP Controlled Room Temperature].

INFORMATION FOR PATIENTS SECTION

The following wording is contained in a separate leaflet provided for patients.

PATIENT INFORMATION LEAFLET

Important Information for Women Who Could Become Pregnant About the Use of Divalproex Sodium Delayed-Release Tablets

Please read this leaflet carefully before you take any of these medications. This leaflet provides a summary of important information about taking these medications to women who could become pregnant. If you have any questions or concerns, or want more information about these medications, contact your doctor or pharmacist.

Information For Women Who Could Become Pregnant

These medications can be obtained only by prescription from your doctor. The decision to use any of these medications is one that you and your doctor should make together, taking into account your individual needs and medical condition.

Before using any of these medications, women who can become pregnant should consider the fact that these medications have been associated with birth defects, in particular, with spina bifida and other defects related to failure of the spinal canal to close normally. Approximately 1 to 2% of children born to women with epilepsy taking divalproex sodium delayed-release tablets in the first 12 weeks of pregnancy had these defects (based on data from the Centers for Disease Control, a U.S. agency based in Atlanta). The incidence in the general population is 0.1 to 0.2%.

These medications have also been associated with other birth defects such as defects of the heart, the bones, and other parts of the body. Information suggests that birth defects may be more likely to occur with these medications than some other drugs that treat your medical condition.

Information For Women Who Are Planning to Get Pregnant

- Women taking any of these medications who are planning to get pregnant should discuss the treatment options with their doctor.

Information For Women Who Become Pregnant

- If you become pregnant while taking any of these medications, you should contact your doctor immediately.

Other Important Information

- Your medication should be taken exactly as prescribed by your doctor to get the most benefit from your medication and reduce the risk of side effects.
- If you have taken more than the prescribed dose of your medication, contact your hospital emergency room or local poison center immediately.
- Your medication was prescribed for your particular condition. Do not use it for another condition or give the drug to others.

Facts About Birth Defects

It is important to know that birth defects may occur even in children of individuals not taking any medications or without any additional risk factors.

This summary provides important information about the use of divalproex sodium delayed-release tablets to women who could become pregnant. If you would like more information about the other potential risks and benefits of these medications, ask your doctor or pharmacist to let you read the professional labeling and then discuss it with them. If you have any questions or concerns about taking these medications, you should discuss them with your doctor.

Call your doctor for medical advice about side effects. You may report side effects to FDA at 1-800-FDA-1088.